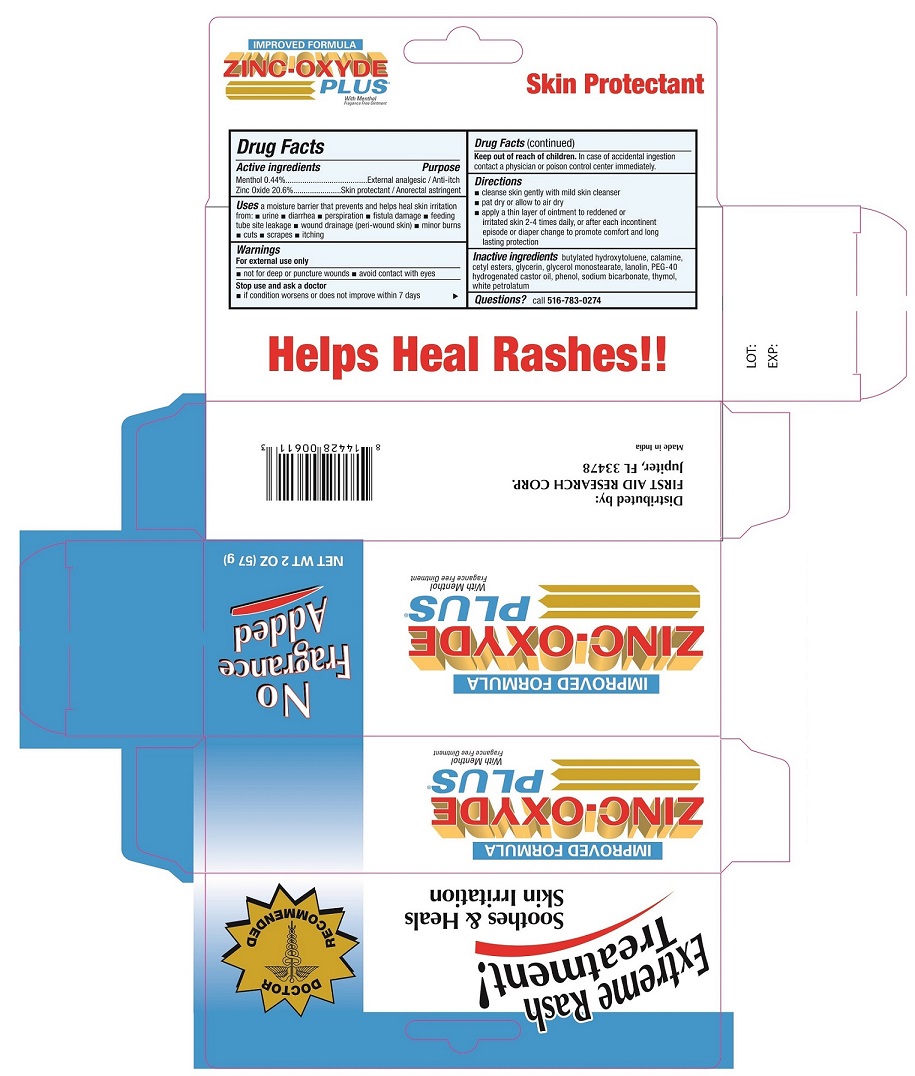 DRUG LABEL: ZINC-OXYDE PLUS
NDC: 75983-006 | Form: OINTMENT
Manufacturer: First Aid Research Corp.
Category: otc | Type: HUMAN OTC DRUG LABEL
Date: 20220224

ACTIVE INGREDIENTS: MENTHOL 4.4 mg/1 g; ZINC OXIDE 206 mg/1 g
INACTIVE INGREDIENTS: BUTYLATED HYDROXYTOLUENE; CETYL ESTERS WAX; GLYCERIN; GLYCERYL MONOSTEARATE; LANOLIN; POLYOXYL 40 HYDROGENATED CASTOR OIL; PHENOL; SODIUM BICARBONATE; THYMOL; PETROLATUM

Zinc Oxide Plus

Active ingredients

Menthol 0.44%

Zinc Oxide 20.6%

Purpose

External analgesic / Anti-itch

Skin protectant / Anorectal astringent

Uses

A moisture barrier that prevents and helps heal skin irritation from: • urine • diarrhea • perspiration • fistula damage • feeding tube site leakage • wound drainage (peri-wound skin) • minor burns • cuts • scrapes • itching

Warnings

For external use only

• not for deep or puncture wounds

• avoid contact with eyes

Stop use and ask a doctor

• if condition worsens or does not improve within 7 days.

Keep out of reach of children. In case of accidental ingestion contact a physician or poison control center immediately.

Directions

- cleanse skin gently with mild skin cleanser
- pat dry or allow to air dry
- apply a thin layer of ointment to reddened or irritated skin 2-4 times daily, or after each incontinent episode or diaper change to promote comfort and long lasting protection.

Inactive ingredients

butylated hydroxytoluene, calamine, cetyl esters, glycerin, glycerol monostearate, lanolin, PEG-40 hydrogenated castor oil, phenol, sodium bicarbonate, thymol, white petrolatum

Questions?

call 516-783-0274